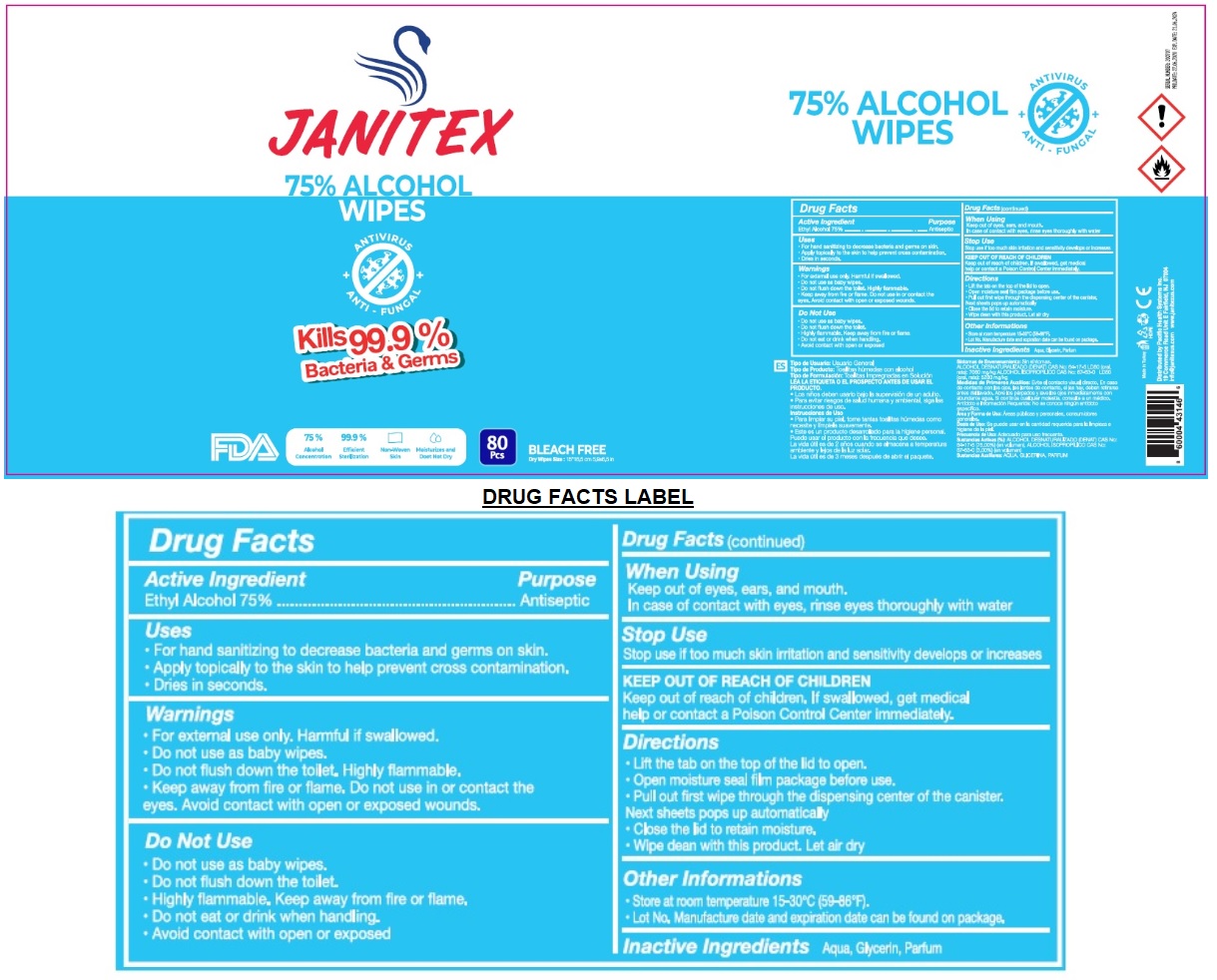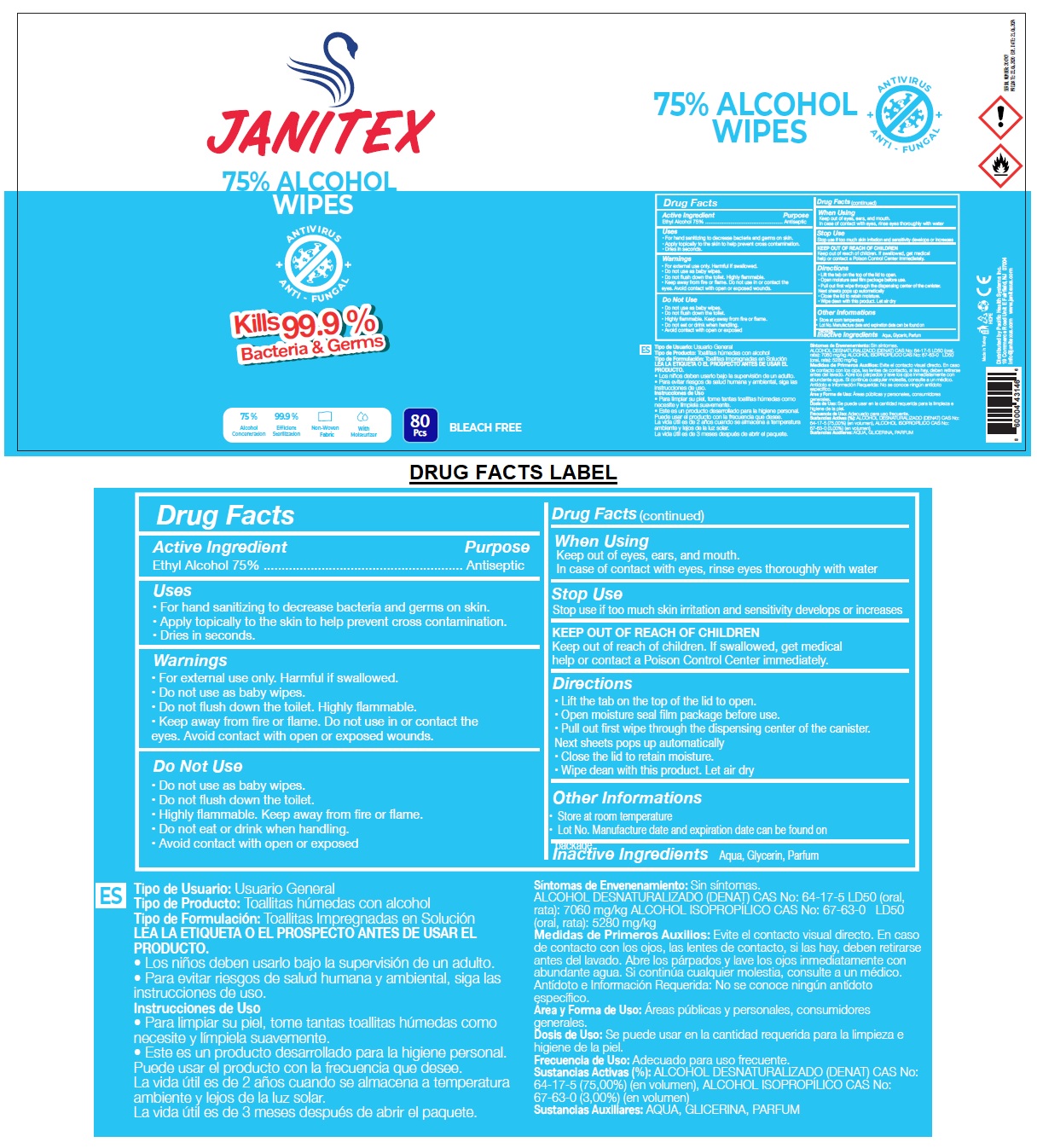 DRUG LABEL: JANITEX
NDC: 79519-020 | Form: CLOTH
Manufacturer: Pacific Health Systems Inc.
Category: otc | Type: HUMAN OTC DRUG LABEL
Date: 20200904

ACTIVE INGREDIENTS: ALCOHOL 75 mL/100 mL
INACTIVE INGREDIENTS: WATER; GLYCERIN

JANITEX 75% ALCOHOL WIPES

Active Ingredient

Ethyl Alcohol 75%

Purpose

Antiseptic

Uses

• For hand sanitizing to decrease bacteria and germs on skin.

• Apply topically to the skin to help prevent cross contamination.

• Dries in seconds.

Warnings

• For external use only. Harmful if swallowed.

• Do not use as baby wipes.

• Do not flush down the toilet.

• Do not use in or contact the eyes.

Do Not Use

• Highly flammable. Keep away from fire or flame.

• Do not eat or drink when handling

• Avoid contact with open or exposed wounds.

When Using

Keep out of eyes, ears, and mouth.

In case of contact with eyes, rinse eyes thoroughly with water

Stop Use

Stop use if too much skin irritation and sensitivity develops or increases

Keep out of reach of children. If swallowed, get medical help or contact a Poison Control Center immediately.

Directions

• Lift the tab on the top of the lid to open.

• Open moisture seal film package before use.

• Pull out first wipe through the dispensing center of the canister.

Next sheets pops up automatically

• Close the lid to retain moisture.

• Wipe clean with this product. Let air dry

Other Informations

• Store at room temperature 15-30℃ (59-86°F).

• Lot No. Manufacture date and expiration date can be found on package.

Inactive Ingredients Aqua, Glycerin, Parfum

ANTIVIRUS

ANTI - FUNGAL

Kills 99.9% Bacteria & Germs

FDA

75% Alcohol Concentration

99.9% Efficient Sterilization

Non-Woven Skin

Moisturizes and Doet Not Dry

BLEACH FREE

Made in Turkey

Distributed by Pacific Health Systems Inc.

19 Commerce Road Unit E Fairfield, NJ 07004

info@janitexus.com www.janitexus.com